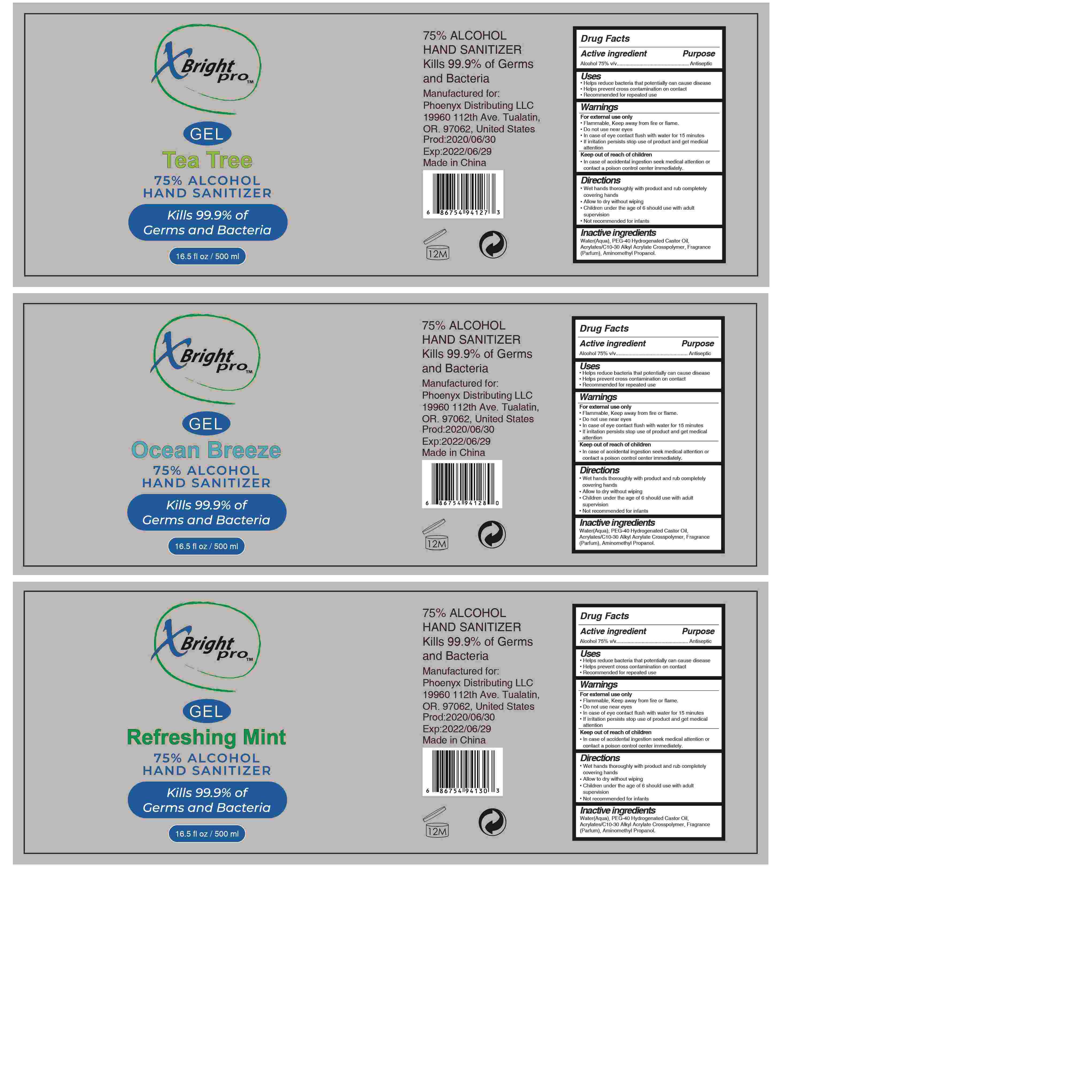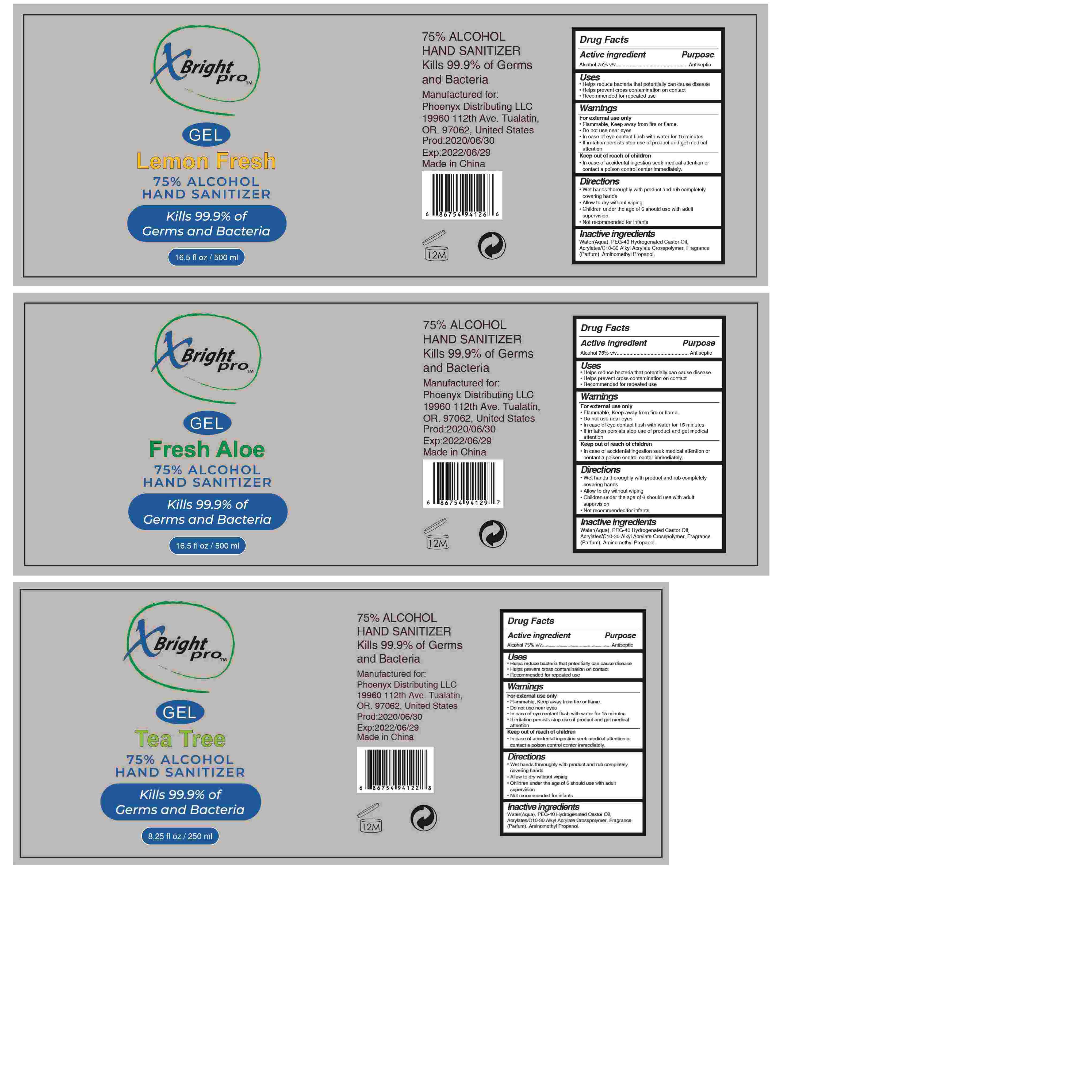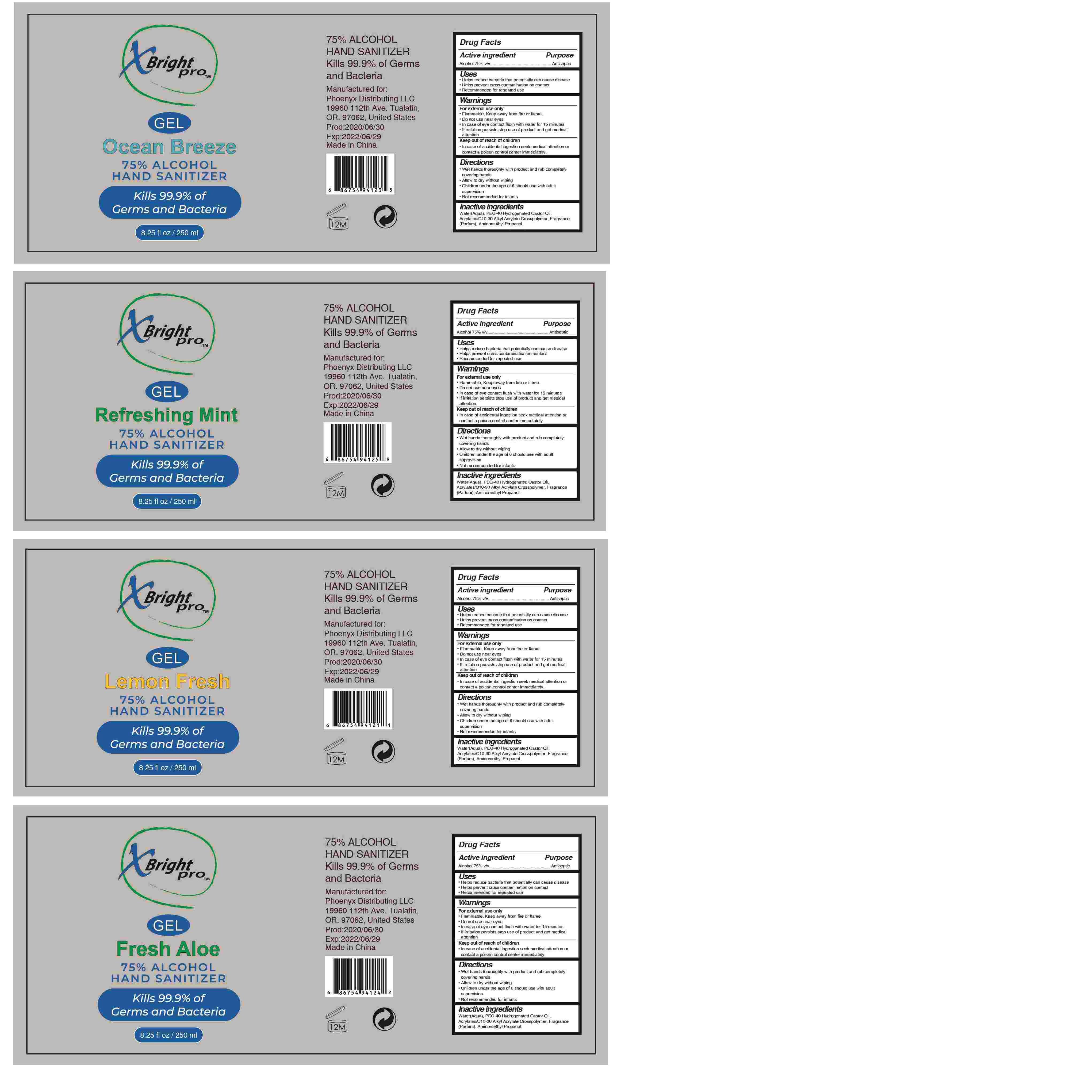 DRUG LABEL: 75% ALCOHOL HAND SANITIZER
NDC: 79316-008 | Form: GEL
Manufacturer: PHOENYX DISTRIBUTING, LLC
Category: otc | Type: HUMAN OTC DRUG LABEL
Date: 20200627

ACTIVE INGREDIENTS: ALCOHOL 75 mL/100 mL
INACTIVE INGREDIENTS: AMINOMETHYLPROPANOL; WATER; CARBOMER INTERPOLYMER TYPE A (55000 CPS); FRAGRANCE LAVENDER & CHIA F-153480; POLYOXYL 40 HYDROGENATED CASTOR OIL

75% ALCOHOL HAND SANITIZER

Active Ingredient(s)

Alcohol 75% v/v.

Purpose

Antiseptic

Use

Helps reduce bacea at pontentially can caus dsease

Helps prevent Cross contamination on contact

Recommended for repeated use

Warnings

For external use only

Flammable, Keep away from fire or flame

Do not use near eyesIn case of eye contact flush with water for 15 minutes

If imitation persists stop use of product and get medical attention

Keep out of reach of childrenIn case of accidental ingestion seek medical attention orcontact a poison contro center immediately

- Do not use in or near the eyes. In case of contact with eyes flush thoroughly with water for 15 minutes

When using this product

Do not use in or near the eyes. In case of contact with eyes flush thoroughly with water

STOP USE

/

Keep out of reach of children. case of accidental ingestion seek medical attention orcontact a poison contro center immediately

Directions

Wet hands thoroughly with product and rub completely Covering hands
Allow to dry without wiping
children under the age of 6 should use with adult supervision
Not recommended for infants

Other information

/

Inactive ingredients

Water(Aqua), PEG-40 Hydrogenated Castor Oil, Acrylates/C10-30 Alkyl Acrylate Crosspolymer,
Fragrance (Parfum) Aminomethyl Propanol